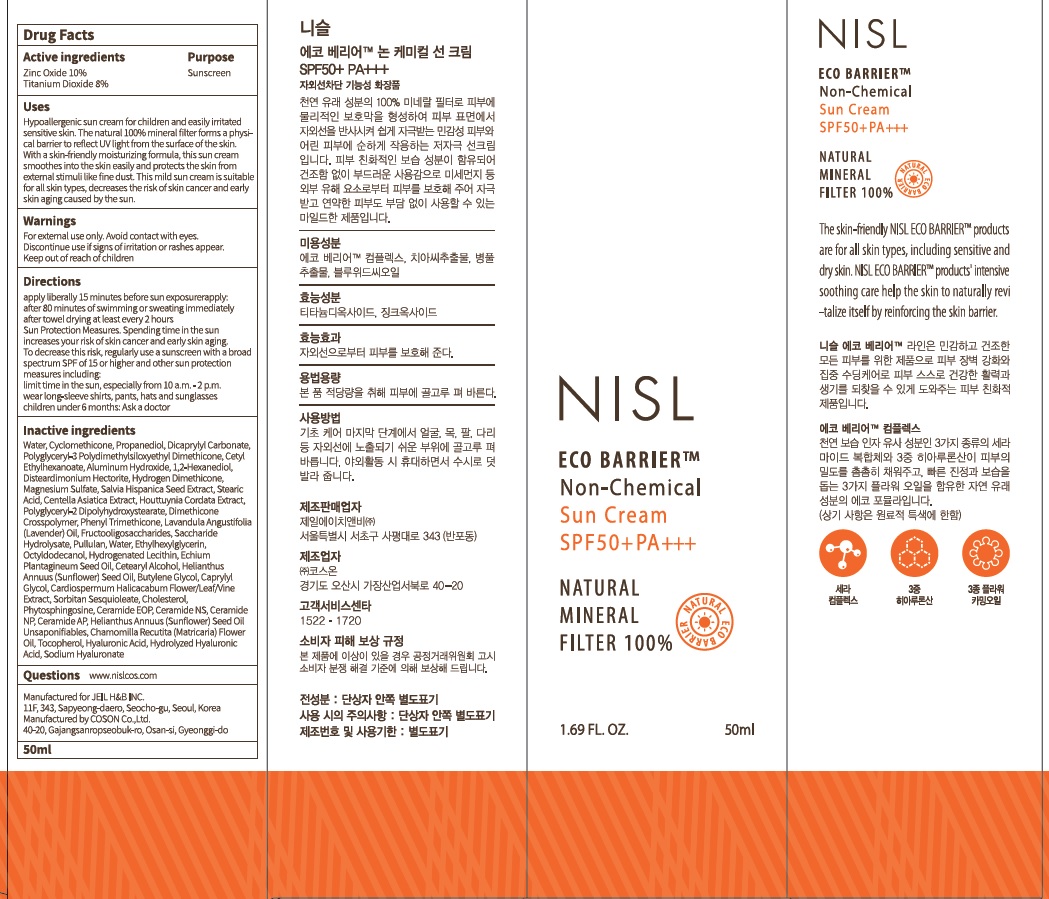 DRUG LABEL: ECO BARRIER NON CHEMICAL SUN
NDC: 71982-010 | Form: CREAM
Manufacturer: JEIL H&B INC.
Category: otc | Type: HUMAN OTC DRUG LABEL
Date: 20180110

ACTIVE INGREDIENTS: Zinc Oxide 5.0 g/50 mL; Titanium Dioxide 4.0 g/50 mL
INACTIVE INGREDIENTS: Water; Propanediol

ACTIVE INGREDIENT

Active ingredients: Zinc Oxide 10%, Titanium Dioxide 8%

INACTIVE INGREDIENT

Inactive ingredients: Water, Cyclomethicone, Propanediol, Dicaprylyl Carbonate, Polyglyceryl-3 Polydimethylsiloxyethyl Dimethicone, Cetyl Ethylhexanoate, Aluminum Hydroxide, 1,2-Hexanediol, Disteardimonium Hectorite, Hydrogen Dimethicone, Magnesium Sulfate, Salvia Hispanica Seed Extract, Stearic Acid, Centella Asiatica Extract, Houttuynia Cordata Extract, Polyglyceryl-2 Dipolyhydroxystearate, Dimethicone Crosspolymer, Phenyl Trimethicone, Lavandula Angustifolia (Lavender) Oil, Fructooligosaccharides, Saccharide Hydrolysate, Pullulan, Water, Ethylhexylglycerin, Octyldodecanol, Hydrogenated Lecithin, Echium Plantagineum Seed Oil, Cetearyl Alcohol, Helianthus Annuus (Sunflower) Seed Oil, Butylene Glycol, Caprylyl Glycol, Cardiospermum Halicacabum Flower/Leaf/Vine Extract, Sorbitan Sesquioleate, Cholesterol, Phytosphingosine, Ceramide EOP, Ceramide NS, Ceramide NP, Ceramide AP, Helianthus Annuus (Sunflower) Seed Oil Unsaponifiables, Chamomilla Recutita (Matricaria) Flower Oil, Tocopherol, Hyaluronic Acid, Hydrolyzed Hyaluronic Acid, Sodium Hyaluronate

PURPOSE

Purpose: Sunscreen

WARNINGS

Warnings: For external use only. Avoid contact with eyes. Discontinue use if signs of irritation or rashes appear. Keep out of reach of children.

DESCRIPTION

Uses: Hypoallergenic sun cream for children and easily irritated sensitive skin. The natural 100% mineral filter forms a physical barrier to reflect UV light from the surface of the skin. With a skin-friendly moisturizing formula, this sun cream smoothes into the skin easily and protects the skin from external stimuli like fine dust. This mild sun cream is suitable for all skin types, decreases the risk of skin cancer and early skin aging caused by the sun.

Directions:

Apply liberally 15 minutes before sun exposure

Reapply: after 80 minutes of swimming or sweating immediately after towel drying at least every 2 hours

Sun Protection Measures. Spending time in the sun increases your risk of skin cancer and early skin aging. To decrease this risk, regularly use a sunscreen with a broad spectrum SPF of 15 or higher and other sun protection measures including: limit time in the sun, especially from 10 a.m. - 2 p.m. wear long-sleeve shirts, pants, hats and sunglasses

Children under 6 months: Ask a doctor

Questions: www.nislcos.com